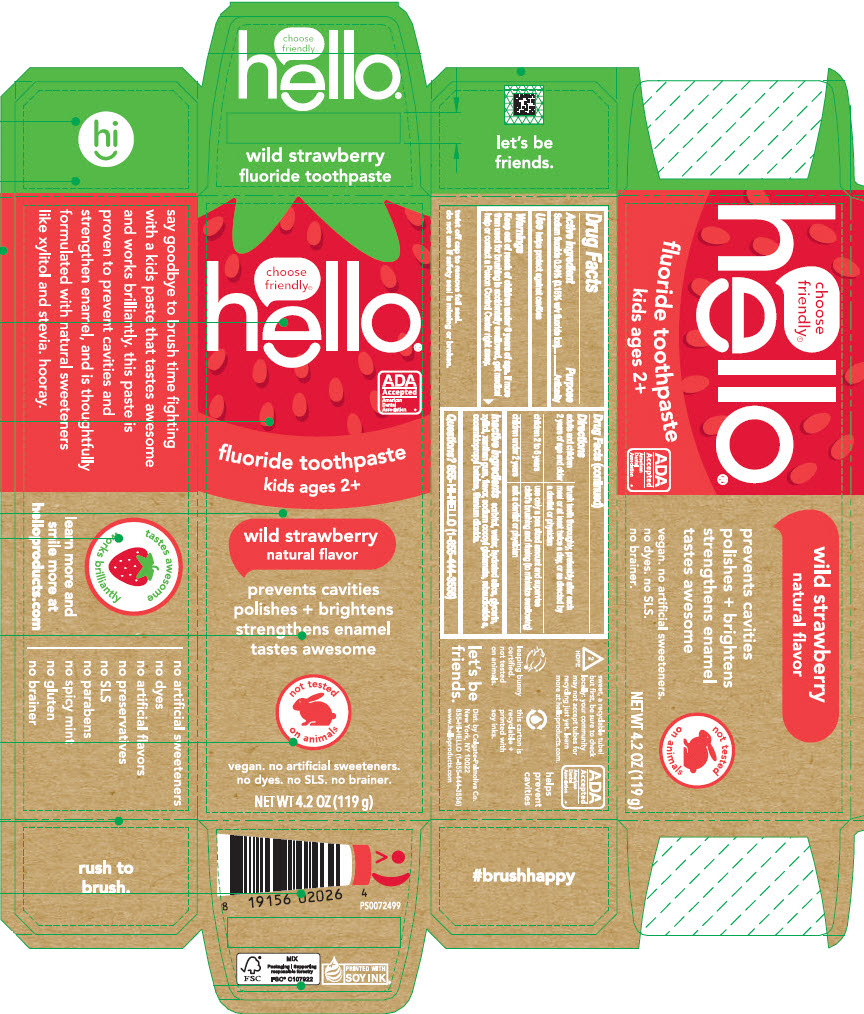 DRUG LABEL: Hello Kids Wild Strawberry
NDC: 35000-688 | Form: PASTE, DENTIFRICE
Manufacturer: Colgate-Palmolive Company
Category: otc | Type: HUMAN OTC DRUG LABEL
Date: 20250415

ACTIVE INGREDIENTS: SODIUM FLUORIDE 1.5 mg/1 g
INACTIVE INGREDIENTS: SORBITOL; HYDRATED SILICA; WATER; GLYCERIN; XYLITOL; XANTHAN GUM; TITANIUM DIOXIDE; COCAMIDOPROPYL BETAINE; SODIUM COCOYL GLUTAMATE; STEVIA REBAUDIUNA LEAF

Hello® Kids Wild Strawberry
Wild Strawberry

Drug Facts

Active ingredient

Sodium fluoride 0.24% (0.15% w/v fluoride ion)

Purpose

Anticavity

Use

helps protect against cavities

Warnings

Keep out of reach of children under 6 years of age.

If more than used for brushing is accidentally swallowed, get medical help or contact a Poison Control Center right away.

Directions

adults and children 2 years of age and older | brush teeth thoroughly, preferably after each meal or at least twice a day, or as directed by a dentist or physician
children 2 to 6 years | use only a pea sized amount and supervise child's brushing and rinsing (to minimize swallowing)
children under 2 years | ask a dentist or physician

Inactive ingredients

sorbitol, hydrated silica, purified water, glycerin, xylitol, xanthan gum, flavor, titanium dioxide, cocamidopropyl betaine, sodium cocoyl glutamate and stevia rebaudiana leaf extract [certified organic] .

Questions?

855-HI-HELLO (1-855-444-3556)

Dist. by Colgate-Palmolive Co.
New York, NY 10022

PRINCIPAL DISPLAY PANEL - 119 g Tube Box

choose
friendly®
hello®

ADA
Accepted
American
Dental
Association ®

fluoride toothpaste
kids ages 2+

wild strawberry
natural flavor

prevents cavities
polishes + brightens
strengthens enamel
tastes awesome

not tested
on animals

vegan. no artificial sweeteners.
no dyes. no SLS. no brainer.

NET WT 4.2 OZ (119 g)